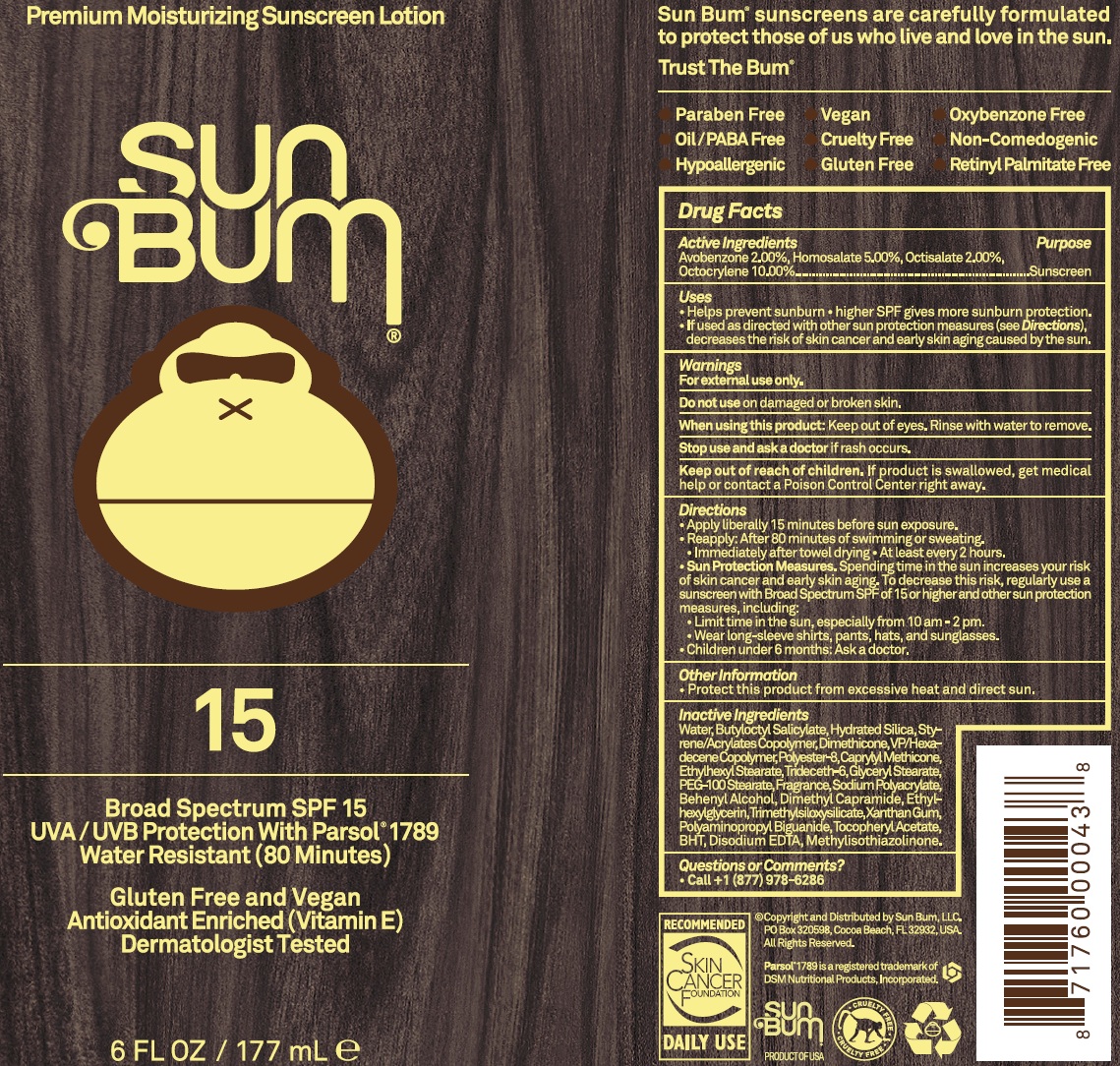 DRUG LABEL: Sun Bum SPF 15 Premium Moisturizing Sunscreen
NDC: 69039-213 | Form: LOTION
Manufacturer: Sun Bum, LLC
Category: otc | Type: HUMAN OTC DRUG LABEL
Date: 20220204

ACTIVE INGREDIENTS: AVOBENZONE 20 mg/1 mL; HOMOSALATE 50 mg/1 mL; OCTISALATE 20 mg/1 mL; OCTOCRYLENE 100 mg/1 mL
INACTIVE INGREDIENTS: WATER; BUTYLOCTYL SALICYLATE; HYDRATED SILICA; DIMETHICONE; VINYLPYRROLIDONE/HEXADECENE COPOLYMER; POLYESTER-8 (1400 MW, CYANODIPHENYLPROPENOYL CAPPED); CAPRYLYL TRISILOXANE; ETHYLHEXYL STEARATE; TRIDECETH-6; GLYCERYL MONOSTEARATE; PEG-100 STEARATE; DOCOSANOL; DIMETHYL CAPRAMIDE; ETHYLHEXYLGLYCERIN; XANTHAN GUM; .ALPHA.-TOCOPHEROL ACETATE; BUTYLATED HYDROXYTOLUENE; EDETATE DISODIUM ANHYDROUS; METHYLISOTHIAZOLINONE

Sun Bum SPF 15 Premium Moisturizing Sunscreen

Active Ingredients

Avobenzone 2.00%, Homosalate 5.00%

Octisalate 2.00%, Octocrylene 10.00%

Purpose

Sunscreen

Uses

- Helps prevent sunburn.
- If used as directed with other sun protection measures (see Directions), decreases the risk of skin cancer and early skin aging caused by the sun.

Warnings

For external use only.

Do not use

on damaged or broken skin.

When using this product:

Keep out of eyes. Rinse with water to remove.

Stop use and ask a doctor

if rash occurs.

Keep out of reach of children .

If product is swallowed, get medical help or contact a Poison Control Center right away.

Directions

- Apply liberally 15 minutes before sun exposure.
- Reapply: After 80 minutes of swimming or sweating.
- Immediately after towel drying.
- At least every 2 hours.
- Sun Protection Measures. Spending time in the sun increases your risk of skin cancer and early skin aging, To decrease this risk, regularly use a sunscreen with a Broad Spectrum SPF of 15 or higher and other sun protection measures, including:
- Limit time in the sun, especially from 10 am - 2 pm.
- Wear long-sleeve shirts, pants, hats, and sunglasses.
- Children under 6 months: Ask a doctor.

Other Information

- Protect this product from excessive heat and direct sun.

Inactive Ingredients

Water, Butyloctyl Salicylate, Hydrated Silica, Styrene/Acrylates Copolymer, Dimethicone, VP/Hexadecene Copolymer, Polyester-8, Caprylyl Methicone, Ethylhexyl Stearate, Trideceth-6, Glyceryl Stearate, PEG-100 Stearate, Fragrance, Sodium Polyacrylate, Behenyl Alcohol, Dimethyl Capramide, Ethylhexylglycerin, Trimethylsiloxysilicate, Xanthan Gum, Polyaminopropyl Biguanide, Tocopheryl Acetate, BHT, Disodium EDTA, Methylisothiazolinone.

Questions or Comments?

Call +1 (877) 978-6286